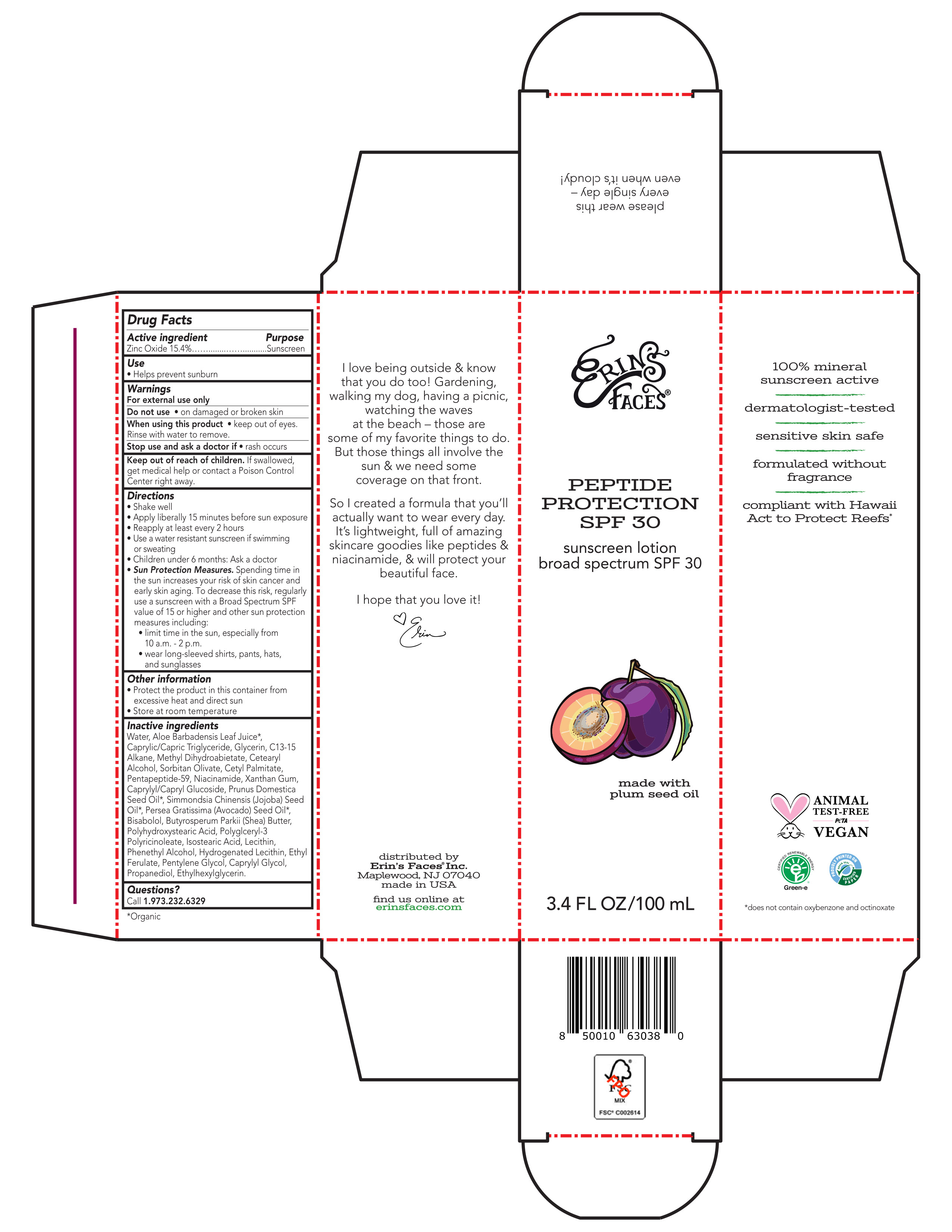 DRUG LABEL: Peptide Protection Broad Spectrum SPF 30 Sunscreen
NDC: 84188-0380 | Form: LOTION
Manufacturer: Erin's Faces Inc
Category: otc | Type: HUMAN OTC DRUG LABEL
Date: 20240506

ACTIVE INGREDIENTS: ZINC OXIDE 154 mg/1 mL
INACTIVE INGREDIENTS: JOJOBA OIL; WATER; LEVOMENOL; MEDIUM-CHAIN TRIGLYCERIDES; ETHYLHEXYLGLYCERIN; SHEA BUTTER; GLYCERIN; PLUM SEED OIL; POLYHYDROXYSTEARIC ACID (2300 MW); ISOSTEARIC ACID; C13-15 ALKANE; CAPRYLYL/CAPRYL OLIGOGLUCOSIDE; AVOCADO SEED; LECITHIN, SOYBEAN; HYDROGENATED SOYBEAN LECITHIN; SORBITAN OLIVATE; METHYL DIHYDROABIETATE; CETOSTEARYL ALCOHOL; XANTHAN GUM; POLYGLYCERYL-3 PENTARICINOLEATE; PENTYLENE GLYCOL; NIACINAMIDE; PROPANEDIOL; ALOE VERA LEAF; CETYL PALMITATE; PHENYLETHYL ALCOHOL; ETHYL FERULATE; CAPRYLYL GLYCOL

Active ingredient

Zinc oxide 15.4%

Purpose

Sunscreen

Use

- Helps prevent sunburn

Warnings

For external use only

Do not use on damaged or broken skin

When using this product keep out of eyes. Rinse with water to remove.

Stop use and ask a doctor if rash occurs

Keep out of reach of children. If swallowed, get medical help or contact a Poison Control Center right away.

Directions

- Shake well
- Apply liberally 15 minutes before sun exposure
- Reapply at least every 2 hours
- Use a water resistant sunscreen if swimming or sweating
- Children under 6 months: Ask a doctor
- Sun Protection Measures. Spending time in the sun increases your risk of skin cancer and early skin aging. To decrease this risk, regularly use a sunscreen with a Broad Spectrum SPF value of 15 or higher and other sun protection measures including:
- limit time in the sun, especially from 10 a.m.–2 p.m.
- wear long-sleeved shirts, pants, hats, and sunglasses

Other information

- Protect the product in this container from excessive heat and direct sun
- Store at room temperature

Inactive ingredients

Water, Aloe Barbadensis Leaf Juice*, Caprylic/Capric Triglyceride, Glycerin, C13-15 Alkane, Methyl Dihydroabietate, Cetearyl Alcohol, Sorbitan Olivate, Cetyl Palmitate, Pentapeptide-59, Niacinamide, Xanthan Gum, Caprylyl/Capryl Glucoside, Prunus Domestica Seed Oil*, Simmondsia Chinensis (Jojoba) Seed Oil*, Persea Gratissima (Avocado) Seed Oil*, Bisabolol, Butyrospermum Parkii (Shea) Butter, Polyhydroxystearic Acid, Polyglceryl-3 Polyricinoleate, Isostearic Acid, Lecithin, Phenethyl Alcohol, Hydrogenated Lecithin, Ethyl Ferulate, Pentylene Glycol, Caprylyl Glycol, Propanediol, Ethylhexylglycerin.

Questions?

Call 1.973.232.6329

*Organic

PRINCIPAL DISPLAY PANEL - 100 mL Pump Bottle in a Carton

ERIN’S FACES®

PEPTIDE PROTECTION SPF 30

sunscreen lotion

broad spectrum SPF 30

made with plum seed oil

3.4 FL OZ/100 mL